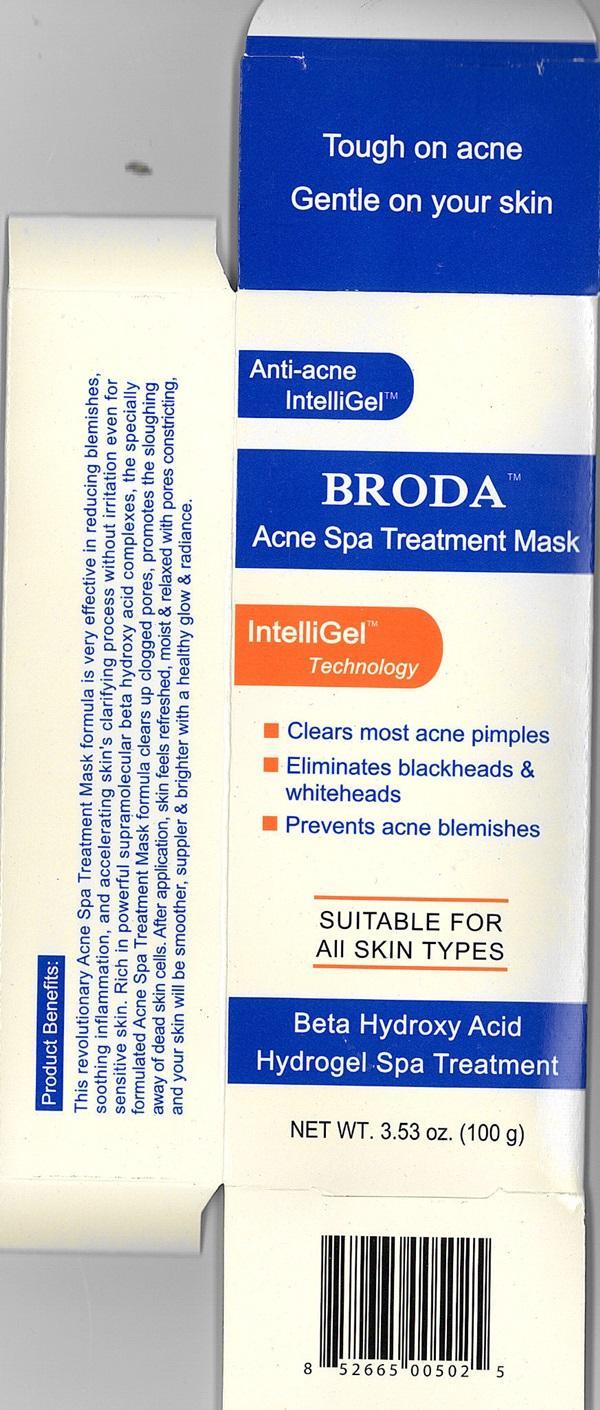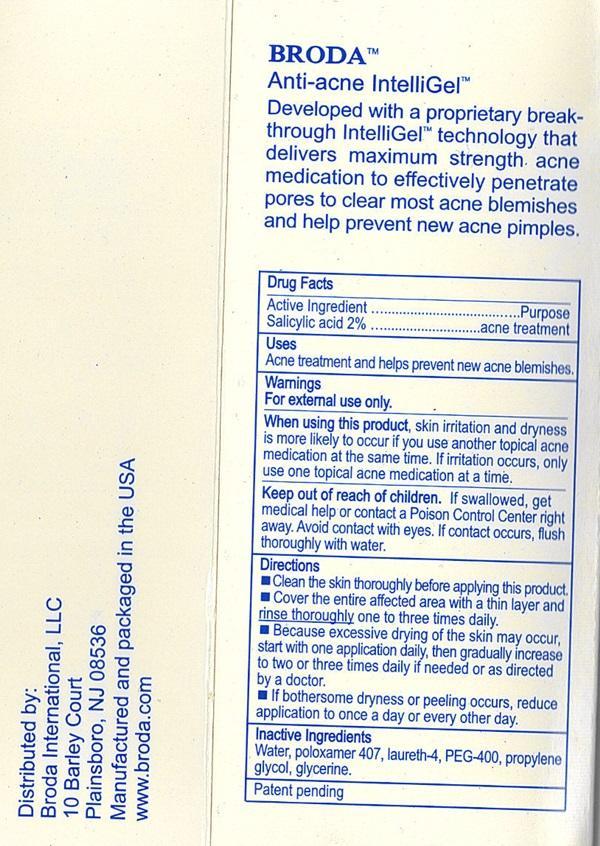 DRUG LABEL: BRODA Acne Spa
NDC: 54111-111 | Form: GEL
Manufacturer: Bentley Laboratories, LLC
Category: otc | Type: HUMAN OTC DRUG LABEL
Date: 20181219

ACTIVE INGREDIENTS: SALICYLIC ACID 2 g/100 g
INACTIVE INGREDIENTS: WATER; POLOXAMER 407; PROPYLENE GLYCOL; POLYETHYLENE GLYCOL 400; LAURETH-4; GLYCERIN

Drug Facts Active Ingredient

Salicylic acid 2%

Purpose

acne treatment

Keep out of reach of children

If swallowed, get medical help or contact a Poison Control Center right away.

Uses

Acne treatment and helps prevent new acne blemishes.

Warnings

For external use only.

When using this product

skin irritation and dryness is more likely to occur if you use another topical acne medication at the same time. If irritation occurs, only use one topical acne medication at a time.
Avoid contact with eyes. If contact occurs, flush thoroughly with water.

Directions

- Clean the skin thoroughly before applying this product.
- Cover the entire affected area with a thin layer and rinse thoroughly one to three times daily.
- Because excessive drying of the skin may occur, start with one application daily, then gradually increase to two or three times daily if needed or as directed by a doctor.
- If bothersome dryness or peeling occurs, reduce application to once a day or every other day.

Inactive ingredients

Water, poloxamer 407, laureth-4, PEG-400, propylene glycol, glycerine.

BRODA Acne Spa Treatment Mask Label

Tough on acne
Gentle on your skin
Anti-acne IntelliGel™
BRODA Acne Spa Treatment Mask
IntelliGel™ Technology
Clears most acne pimples
Eliminates blackheads and whiteheads
Prevents acne blemishes

SUITABLE FOR ALL SKIN TYPES

Beta Hydroxy Acid
Hydrogel Spa Treatment

NET WT. 3.53 oz. (100 g)

Product Benefits:
This revolutionary Acne Spa Treatment Mask formula is very effective in reducing blemishes, soothing inflammation, and accelerating skin's clarifying process without irritation even for sensitive skin. Rich in powerful supramolecular beta hydroxy acid complexes, the specially formulated Acne Spa Treatment Mask formula clears up clogged pores, promotes the sloughing away of dead skin cells. After application, skin feels refreshed, moist and relaxed with pores constricting, and your skin will be smoother, suppler and bright with a healthy glow and radiance.

Distributed by:
Broda International, LLC
10 Barley Court
Plainsboro, NJ 08536
Manufactured and packaged in the USA
www.broda.com
Patent pending
BRODA™
Anti-acne IntelliGel™
Developed with a proprietary break-through IntellGel™ technology that delivers maximum strength acne medication to effectively penetrate pores to clear most acne blemishes and help prevent new acne pimples.